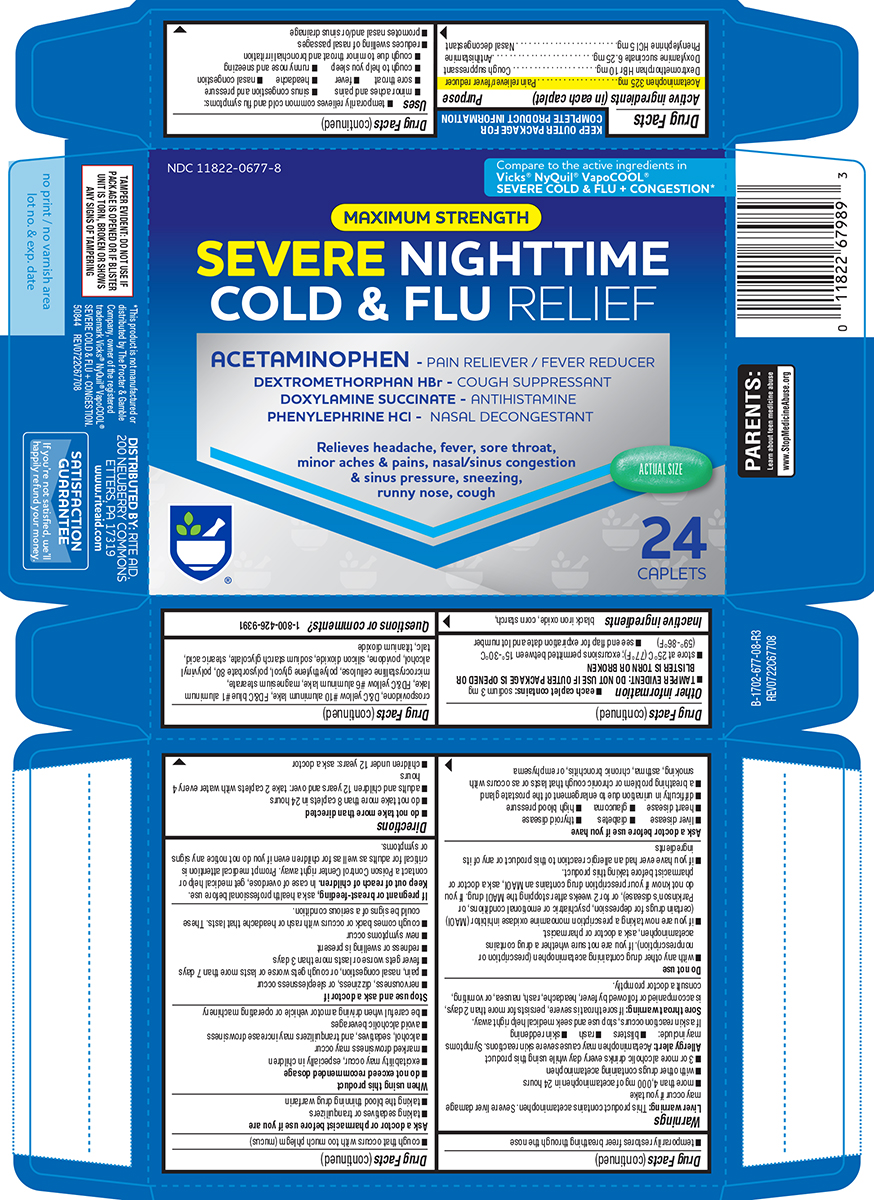 DRUG LABEL: Severe Nighttime Cold and Flu Relief
NDC: 11822-0677 | Form: TABLET, FILM COATED
Manufacturer: Rite Aid Corporation
Category: otc | Type: HUMAN OTC DRUG LABEL
Date: 20250819

ACTIVE INGREDIENTS: ACETAMINOPHEN 325 mg/1 1; DEXTROMETHORPHAN HYDROBROMIDE 10 mg/1 1; DOXYLAMINE SUCCINATE 6.25 mg/1 1; PHENYLEPHRINE HYDROCHLORIDE 5 mg/1 1
INACTIVE INGREDIENTS: FERROSOFERRIC OXIDE; STARCH, CORN; CROSPOVIDONE, UNSPECIFIED; D&C YELLOW NO. 10 ALUMINUM LAKE; FD&C BLUE NO. 1 ALUMINUM LAKE; FD&C YELLOW NO. 6 ALUMINUM LAKE; MAGNESIUM STEARATE; MICROCRYSTALLINE CELLULOSE; POLYETHYLENE GLYCOL, UNSPECIFIED; POLYSORBATE 80; POLYVINYL ALCOHOL, UNSPECIFIED; POVIDONE, UNSPECIFIED; SILICON DIOXIDE; SODIUM STARCH GLYCOLATE TYPE A POTATO; STEARIC ACID; TALC; TITANIUM DIOXIDE

Rite Aid 44-677

Active ingredients (in each caplet)

Acetaminophen 325 mg
Dextromethorphan HBr 10 mg
Doxylamine succinate 6.25 mg
Phenylephrine HCl 5 mg

Purpose

Pain reliever/fever reducer
Cough suppressant
Antihistamine
Nasal decongestant

Uses

- temporarily relieves common cold and flu symptoms:
  - minor aches and pains
  - sinus congestion and pressure
  - sore throat
  - fever
  - headache
  - nasal congestion
  - cough to help you sleep
  - runny nose and sneezing
  - cough due to minor throat and bronchial irritation
- reduces swelling of nasal passages
- promotes nasal and/or sinus drainage
- temporarily restores freer breathing through the nose

Warnings

Liver warning: This product contains acetaminophen. Severe liver damage may occur if you take

- more than 4,000 mg of acetaminophen in 24 hours
- with other drugs containing acetaminophen
- 3 or more alcoholic drinks every day while using this product

Allergy alert: Acetaminophen may cause severe skin reactions. Symptoms may include:

- blisters
- rash
- skin reddening

If a skin reaction occurs, stop use and seek medical help right away.

Sore throat warning: If sore throat is severe, persists for more than 2 days, is accompanied or followed by fever, headache, rash, nausea, or vomiting, consult a doctor promptly.

Do not use

- with any other drug containing acetaminophen (prescription or nonprescription). If you are not sure whether a drug contains acetaminophen, ask a doctor or pharmacist.
- if you are now taking a prescription monoamine oxidase inhibitor (MAOI) (certain drugs for depression, psychiatric or emotional conditions, or Parkinson’s disease), or for 2 weeks after stopping the MAOI drug. If you do not know if your prescription drug contains an MAOI, ask a doctor or pharmacist before taking this product.
- if you have ever had an allergic reaction to this product or any of its ingredients

Ask a doctor before use if you have

- liver disease
- diabetes
- thyroid disease
- heart disease
- glaucoma
- high blood pressure
- difficulty in urination due to enlargement of the prostate gland
- a breathing problem or chronic cough that lasts or as occurs with smoking, asthma, chronic bronchitis, or emphysema
- cough that occurs with too much phlegm (mucus)

Ask a doctor or pharmacist before use if you are

- taking sedatives or tranquilizers
- taking the blood thinning drug warfarin

When using this product

- do not exceed recommended dosage
- excitability may occur, especially in children
- marked drowsiness may occur
- alcohol, sedatives, and tranquilizers may increase drowsiness
- avoid alcoholic beverages
- be careful when driving a motor vehicle or operating machinery

Stop use and ask a doctor if

- nervousness, dizziness, or sleeplessness occur
- pain, nasal congestion, or cough gets worse or lasts more than 7 days
- fever gets worse or lasts more than 3 days
- redness or swelling is present
- new symptoms occur
- cough comes back or occurs with rash or headache that lasts. These could be signs of a serious condition.

If pregnant or breast-feeding,

ask a health professional before use.

Keep out of reach of children.

In case of overdose, get medical help or contact a Poison Control Center right away. Prompt medical attention is critical for adults as well as for children even if you do not notice any signs or symptoms.

Directions

- do not take more than directed
- do not take more than 8 caplets in 24 hours
- adults and children 12 years and over: take 2 caplets with water every 4 hours
- children under 12 years: ask a doctor

Other information

- each caplet contains: sodium 3 mg
- TAMPER EVIDENT: DO NOT USE IF OUTER PACKAGE IS OPENED OR BLISTER IS TORN OR BROKEN
- store at 25°C (77°F); excursions permitted between 15°-30°C (59°-86°F)
- see end flap for expiration date and lot number

Inactive ingredients

black iron oxide, corn starch, crospovidone, D&C yellow #10 aluminum lake, FD&C blue #1 aluminum lake, FD&C yellow #6 aluminum lake, magnesium stearate, microcrystalline cellulose, polyethylene glycol, polysorbate 80, polyvinyl alcohol, povidone, silicon dioxide, sodium starch glycolate, stearic acid, talc, titanium dioxide

Questions or comments?

1-800-426-9391

Principal display panel

NDC 11822-0677-8

Compare to the active ingredients in
Vicks® NyQuil® VapoCOOL®
SEVERE COLD & FLU + CONGESTION*

MAXIMUM STRENGTH

SEVERE NIGHTTIME
COLD & FLU RELIEF

DEXTROMETHORPHAN HBr - COUGH SUPPRESSANT
DOXYLAMINE SUCCINATE - ANTIHISTAMINE
PHENYLEPHRINE HCl - NASAL DECONGESTANT

Relieves headache, fever, sore throat,
minor aches & pains, nasal/sinus congestion
& sinus pressure, sneezing, runny nose, cough

Actual Size

24 CAPLETS

TAMPER EVIDENT: DO NOT USE IF
PACKAGE IS OPENED OR IF BLISTER
UNIT IS TORN, BROKEN OR SHOWS
ANY SIGNS OF TAMPERING

*This product is not manufactured or
distributed by The Procter & Gamble
Company, owner of the registered
trademark Vicks® NyQuil® VapoCOOL®
SEVERE COLD & FLU + CONGESTION.
50844 REV0722C67708

DISTRIBUTED BY: RITE AID,
200 NEWBERRY COMMONS
ETTERS, PA 17319
www.riteaid.com

SATISFACTION
GUARANTEE
If you're not satisfied,
we'll happily refund your money.

Rite Aid 44-677